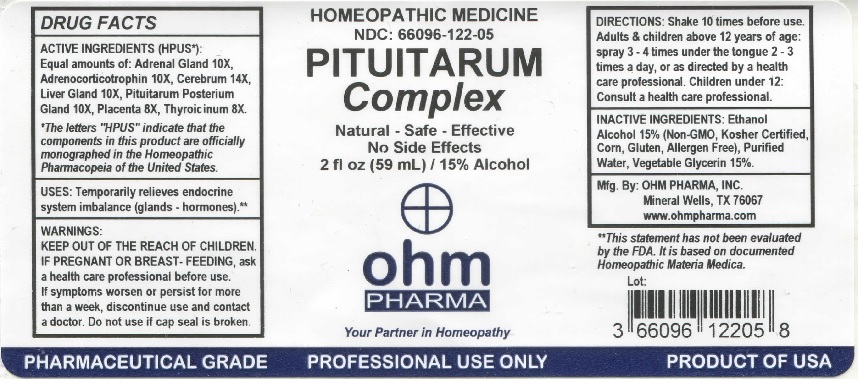 DRUG LABEL: OHM Pituitarum Complex
NDC: 66096-122 | Form: LIQUID
Manufacturer: OHM PHARMA INC.
Category: homeopathic | Type: HUMAN PRESCRIPTION DRUG LABEL
Date: 20211229

ACTIVE INGREDIENTS: EPINEPHRINE 10 [hp_X]/59 mL; CORTICOTROPIN 10 [hp_X]/59 mL; SUS SCROFA CEREBRUM 14 [hp_X]/59 mL; SUS SCROFA ADRENAL GLAND 10 [hp_X]/59 mL; SUS SCROFA PITUITARY GLAND, POSTERIOR 10 [hp_X]/59 mL; SUS SCROFA PLACENTA 8 [hp_X]/59 mL; THYROID, UNSPECIFIED 8 [hp_X]/59 mL
INACTIVE INGREDIENTS: ALCOHOL; WATER; GLYCERIN

OHM Pituitarum Complex

ACTIVE INGREDIENT

ACTIVE INGREDIENTS (HPUS*): Equal amounts of: Adrenal Gland 10X, Adrenocorticotrophin 10X, Cerebrum 14X, Liver Gland 10X, Pituitarum Posterium Gland 10X, Placenta 8X, Thyroidinum 8X.

*The letters "HPUS" indicate that the components in this product are officially monographed in the Homeopathic Pharmacopeia of the United States.

INDICATIONS AND USAGE

USES: Temporarily relieves endocrine system imbalance (glands - hormones).**

**This statement has not been evaluated by the FDA. It is based on documented Homeopathic Materia Medica.

WARNINGS

WARNINGS: IF PREGNANT OR BREAST-FEEDING, ask a health care professional before use. if symptoms worsen or persist for more than a week, discontinue use and contact a doctor.

- KEEP OUT OF REACH OF CHILDREN.

DOSAGE AND ADMINISTRATION

DIRECTIONS: Shake 10 times before use. Adults & children above 12 years of age: spray 3-4 times under the tongue 2-3 times a day, or as directed by a health care professional. Children under 12: Consult a health care professional.

Do not use if cap seal is broken.

INACTIVE INGREDIENT

INACTIVE INGREDIENTS: Ethanol Alcohol 15% (Non-GMO, Kosher Certified, Corn, Gluten, Allergen Free), Purified Water, Vegetable Glycerin 15%.

QUESTIONS

Mfg. By: OHM PHARMA, INC. Mineral Wells, TX 76067

www.ohmpharma.com

PACKAGE LABEL

HOMEOPATHIC MEDICINE

PITUITARUM Complex

Natural - Safe - Effective

No Side Effects

2 fl oz (59 mL) / 15% Alcohol

PRODUCT OF USA

Relieves endocrine system imbalance.